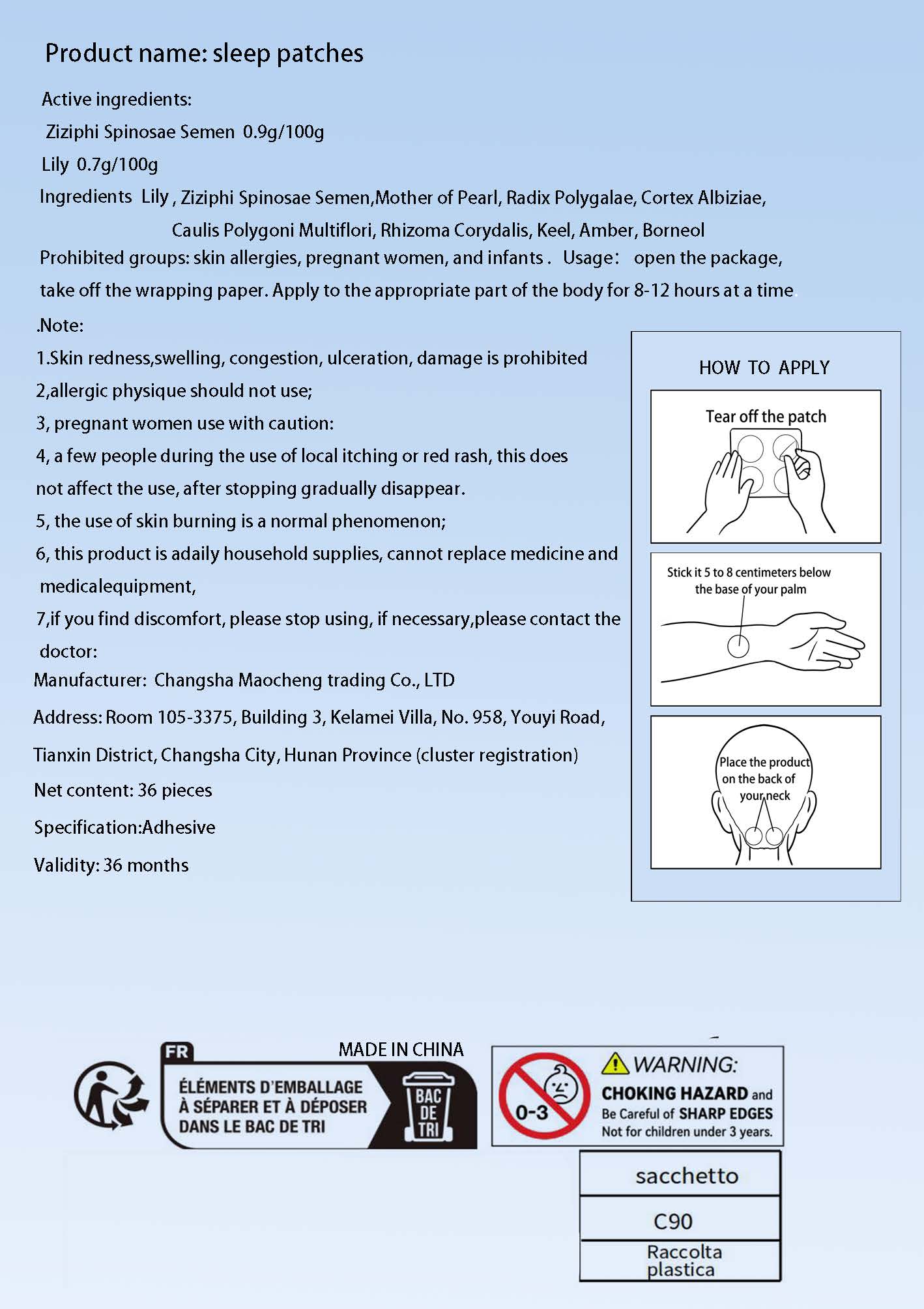 DRUG LABEL: sleep patches
NDC: 84876-001 | Form: PATCH
Manufacturer: Changsha Maocheng Trading Co., Ltd
Category: otc | Type: HUMAN OTC DRUG LABEL
Date: 20251229

ACTIVE INGREDIENTS: LILIUM PUMILUM BULB 0.7 g/100 h; JUJUBE SEED 0.9 g/100 h
INACTIVE INGREDIENTS: AMBER; ALBIZIA JULIBRISSIN WHOLE; BORNEOL; POLYGALA SIBIRICA ROOT; MAMMAL BONE, FOSSILIZED; GRAPTOPETALUM PARAGUAYENSE WHOLE; CORYDALIS YANHUSUO WHOLE

ACTIVE INGREDIENT

Active ingredients:Ziziphi Spinosae Semen 0.9g/100gLily 0.7g/100g

INACTIVE INGREDIENT

Mother of Pearl, Radix Polygalae, Cortex Albiziae.Caulis Polygoni Multiflori, Rhizoma Corydalis, Keel, Amber, Borneol

PURPOSE

Improve sleep

WARNINGS

Prohibited groups: skin allergies, pregnant women, and infants

STOP USE

1.Skin redness,swelling, congestion, ulceration, damage is prohibited
2,allergic physique should not use;
3, pregnant women use with caution:
4, a few people during the use oflocal itching or red rash, this doesnot affect the use, after stopping gradually disappear.5, the use of skin burning is a normal phenomenon;6, this product is adaily household supplies, cannot replace medicine andmedicalequipment,
7,if you find discomfort, please stop using, if necessary,please contact the
doctor

DO NOT USE

1.Skin redness,swelling, congestion, ulceration, damage is prohibited
2,allergic physique should not use;
3, pregnant women use with caution:
4, a few people during the use oflocal itching or red rash, this doesnot affect the use, after stopping gradually disappear.5, the use of skin burning is a normal phenomenon;6, this product is adaily household supplies, cannot replace medicine andmedicalequipment,
7,if you find discomfort, please stop using, if necessary,please contact the
doctor

WHEN USING

Apply to the appropriate part of the body for 8-12 hours at a time

keep out of reach of children

INDICATIONS AND USAGE

Tear off the patch,Stick it 5 to 8 centimeters belowthe base of your palm,
Place the product on the back of your neck

DOSAGE AND ADMINISTRATION

Apply to the appropriate part of the body for 8-12 hours at a time